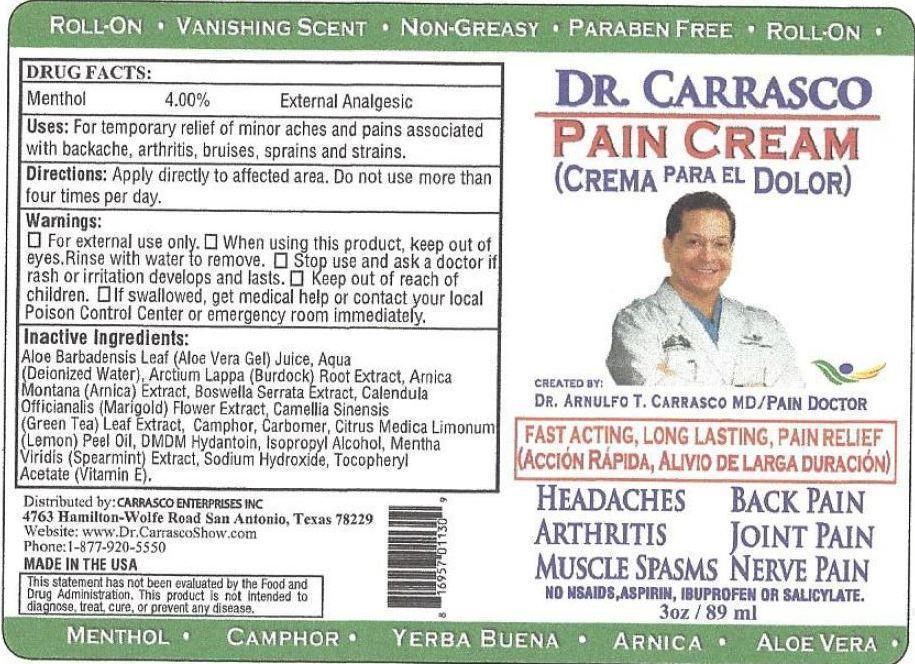 DRUG LABEL: Dr. Carrasco Pain Relief
NDC: 69921-024 | Form: CREAM
Manufacturer: Carrasco Enterprises, Inc.
Category: otc | Type: HUMAN OTC DRUG LABEL
Date: 20231110

ACTIVE INGREDIENTS: MENTHOL 40 mg/1 mL
INACTIVE INGREDIENTS: ALOE VERA LEAF; WATER; ARCTIUM LAPPA ROOT; ARNICA MONTANA; GREEN TEA LEAF; DMDM HYDANTOIN; ISOPROPYL ALCOHOL; MENTHA SPICATA; SODIUM HYDROXIDE; .ALPHA.-TOCOPHEROL ACETATE

Dr. Carrasco Pain Relief

Active Ingredient

Menthol 4.00%

Purpose Section

External Analgesic

Uses

For temporary relief of minor aches and pains associated with backache, arthritis, bruises, sprains and strains.

Directions

Apply directly to affected area. Do not use more than four times per day.

Warnings

For external use only.

When using this product

keep out of eyes. Rinse with water to remove.

Stop use and ask a doctor

if rash or irritation develops and last.

Keep out of reach of children.

If swallowed , get medical help or contact your local poison Control Center or emergency room immediately.

Inactive Ingredients

Aloe Barbadensis Leaf (Aloe Vera Gel) Juice, Aqua (Deionized Water), Arctium Lappa (Burdock) Root Extract, Arnica Montana (Arnica) Extract, Boswella Serrata Extract, Calendula Officianalis (Marigold) Flower Extract, Camellia Sinensis (Green Tea) Leaf Extract, Camphor, Carbomer, Citrus Medica Limonum (Lemon) Peel Oil, Dmdm Hydantoin, Isopropyl Alcohol, Mentha Viridis (Spearmint) Extract, Sodium Hydroxide, Tocopheryl Acetate (Vitamin E).